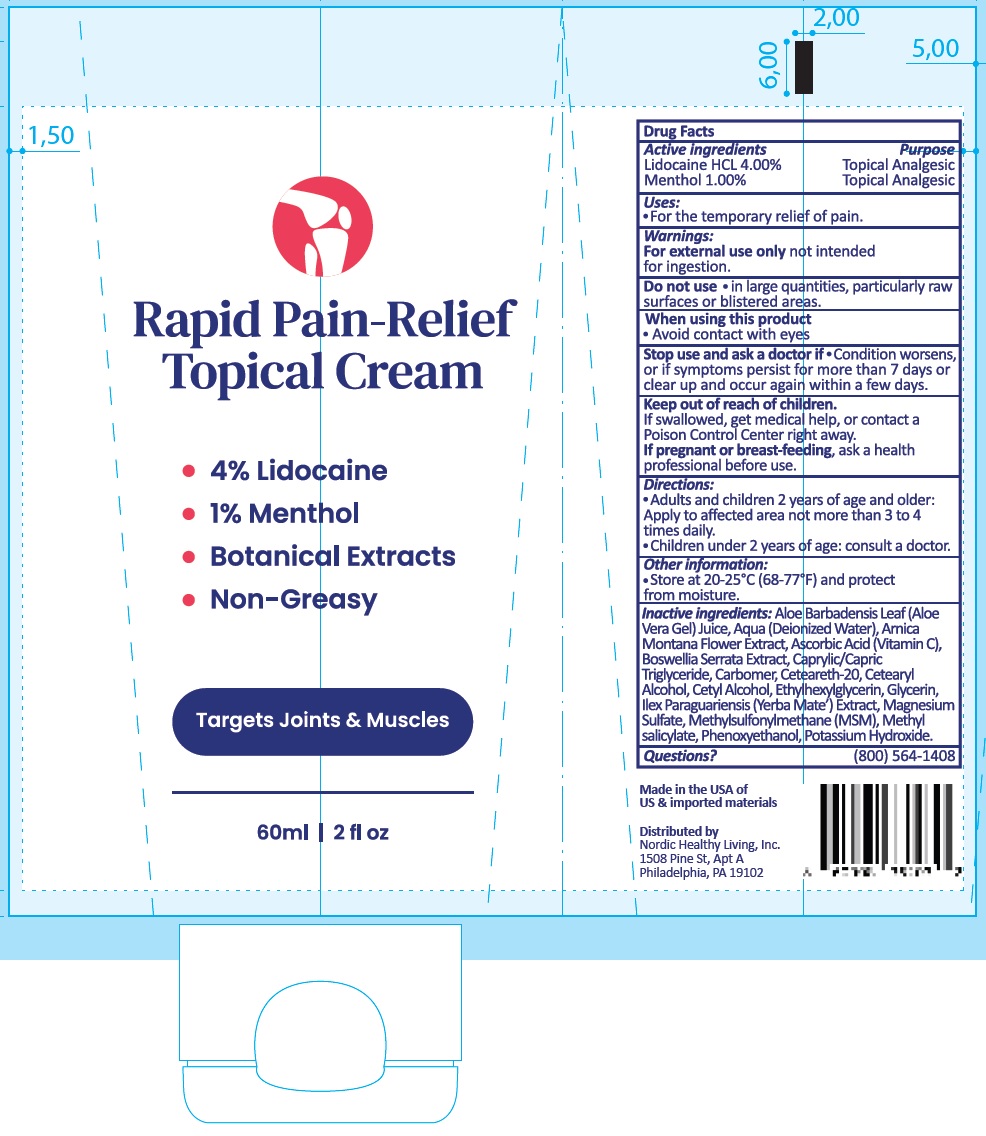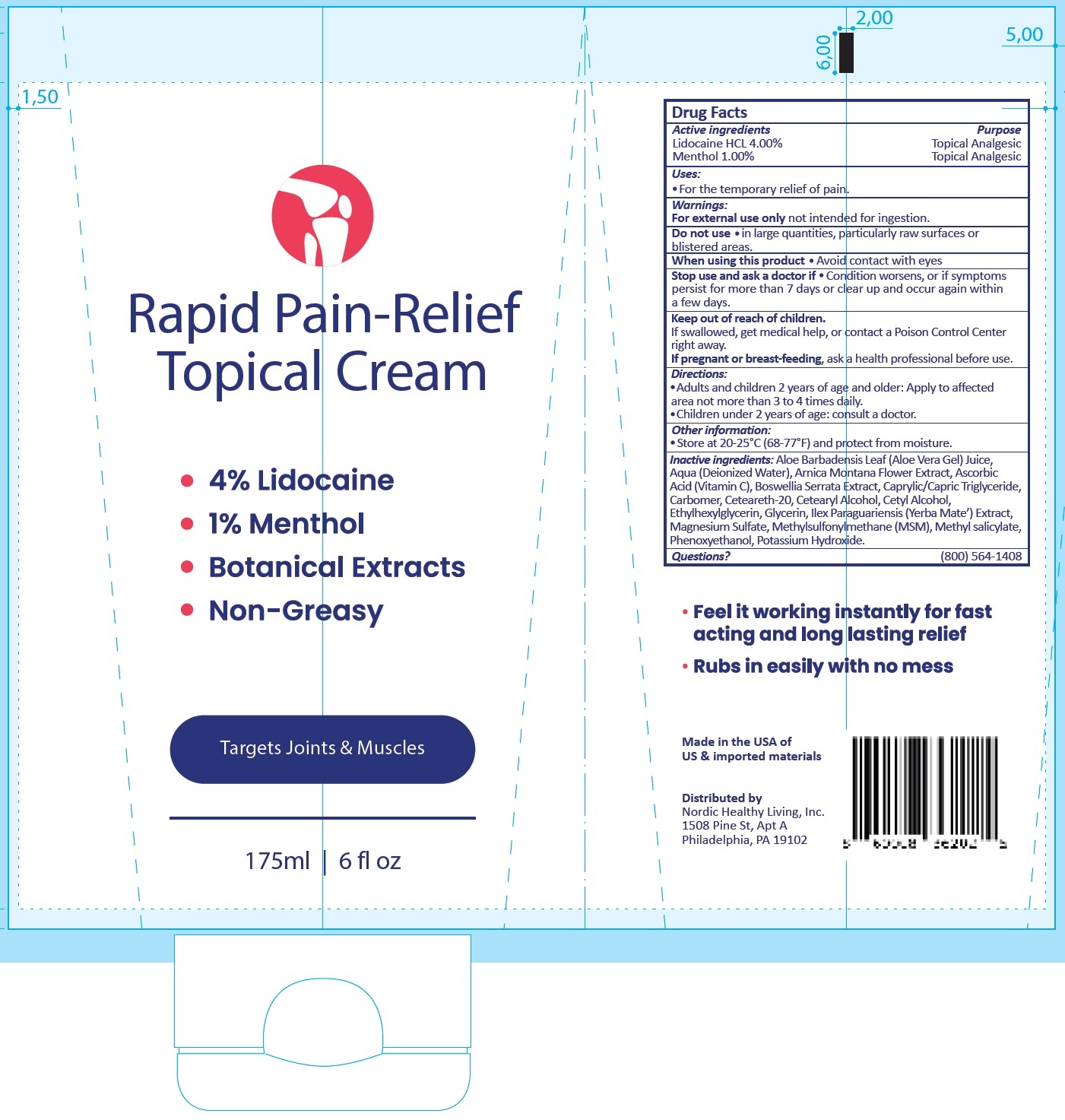 DRUG LABEL: RAPID PAIN-RELIEF TOPICAL
NDC: 82798-295 | Form: CREAM
Manufacturer: NORDIC HEALTHY LIVING INC.
Category: otc | Type: HUMAN OTC DRUG LABEL
Date: 20231106

ACTIVE INGREDIENTS: LIDOCAINE HYDROCHLORIDE 40 mg/1 mL; MENTHOL 10 mg/1 mL
INACTIVE INGREDIENTS: ALOE VERA LEAF; WATER; ARNICA MONTANA FLOWER; ASCORBIC ACID; INDIAN FRANKINCENSE; MEDIUM-CHAIN TRIGLYCERIDES; CARBOMER HOMOPOLYMER, UNSPECIFIED TYPE; POLYOXYL 20 CETOSTEARYL ETHER; CETOSTEARYL ALCOHOL; CETYL ALCOHOL; ETHYLHEXYLGLYCERIN; GLYCERIN; ILEX PARAGUARIENSIS LEAF; MAGNESIUM SULFATE, UNSPECIFIED FORM; DIMETHYL SULFONE; METHYL SALICYLATE; PHENOXYETHANOL; POTASSIUM HYDROXIDE

RAPID PAIN-RELIEF TOPICAL CREAM

Active ingredients

Lidocaine HCL 4.00% Menthol 1.00%

Purpose

Topical Analgesic

Uses:

- For the temporary relief of pain.

Warnings:

not intended for ingestion. For external use only

Do not use

- in large quantities, particularly raw surfaces or blistered areas.

When using this product

- Avoid contact with eyes

Stop use and ask a doctor if

Condition worsens, or if symptoms persist for more than 7 days or clear up and occur again within a few days.

Keep out of reach of children.

If swallowed, get medical help, or contact a Poison Control Center right away.

If pregnant or breast-feeding,

ask a health professional before use.

Directions:

- Adults and children 2 years of age and older: Apply to affected area not more than 3 to 4 times daily.
- Children under 2 years of age: consult a doctor.

Other information:

- Store at 20-25°C (68-77°F) and protect from moisture.

Inactive ingredients:

Aloe Barbadensis Leaf (Aloe Vera Gel) Juice, Aqua (Deionized Water), Arnica Montana Flower Extract, Ascorbic Acid (Vitamin C), Boswellia Serrata Extract, Caprylic/Capric Triglyceride, Carbomer, Ceteareth-20, Cetearyl Alcohol, Cetyl Alcohol, Ethylhexylglycerin, Glycerin, Ilex Paraguariensis (Yerba Mate’) Extract, Magnesium Sulfate, Methylsulfonylmethane (MSM), Methyl salicylate, Phenoxyethanol, Potassium Hydroxide.

Questions?

(800) 564-1408